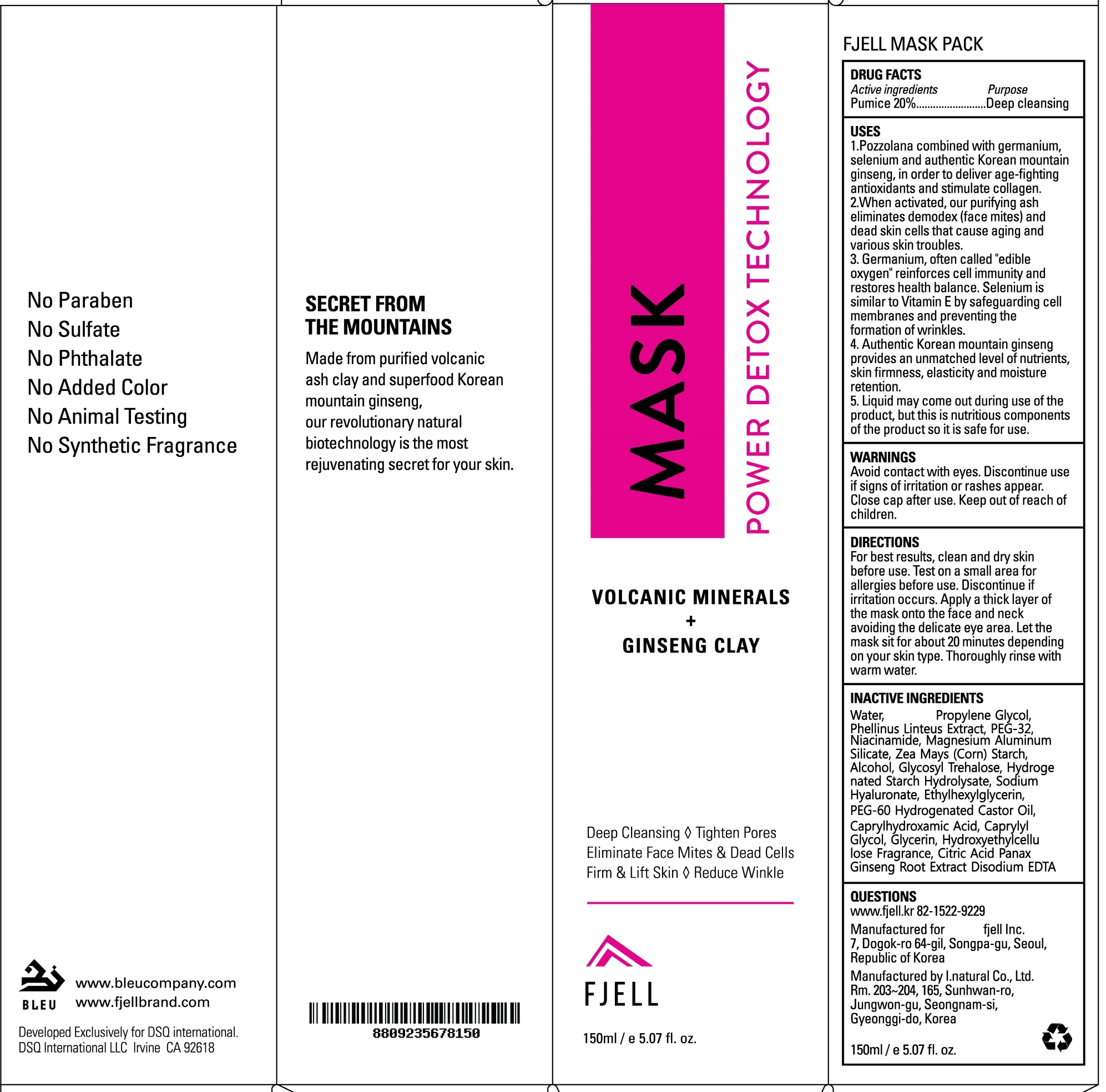 DRUG LABEL: Fjell Mask Pack
NDC: 72194-010 | Form: CREAM
Manufacturer: Fjell INC.
Category: otc | Type: HUMAN OTC DRUG LABEL
Date: 20180329

ACTIVE INGREDIENTS: Pumice 30.0 g/150 mL
INACTIVE INGREDIENTS: Water; Propylene Glycol

ACTIVE INGREDIENT

Active ingredients: Pumice 20%

INACTIVE INGREDIENT

Inactive ingredients: Water, Propylene Glycol, Phellinus Linteus Extract, PEG-32, Magnesium Aluminum Silicate, Zea Mays (Corn) Starch, Alcohol, Glycosyl Trehalose, Hydrogenated Starch Hydrolysate, Sodium Hyaluronate, Ethylhexylglycerin, PEG-60 Hydrogenated Castor Oil, Caprylhydroxamic Acid, Caprylyl Glycol, Glycerin, Hydroxyethylcellulose, Fragrance, Citric Acid, Panax Ginseng Root Extract, Disodium EDTA, Niacinamide

PURPOSE

Purpose: Deep cleansing

WARNINGS

Warnings: Avoid contact with eyes. Discontinue use if signs of irritation or rashes appear. Replace the cap after use. Keep out of reach of children.

KEEP OUT OF REACH OF CHILDREN

Uses

1. Pozzolana combined with germanium, selenium and authentic Korean mountain ginseng, in oder to deliver age-fighting antioxidants and stimulate collagen.

2. When activated, our purifying ash eliminates demodex(face mites) and dead skin cells that cause aging and various skin troubles.

3. Germanium, often called "edible oxygen" reinforces cell immunity and restores health balance. Selenium is similar to Vitamin E by safeguarding cell membranes and preventing the formation of wrinkles.

4. Authentic Korean mountain ginseng provides an unmatched level of nutrients, skin firmness, elasticity and moisture retention.

5. Liquid may come out during use of the product, but this is nutritious components of the product so it is safe for use.

Directions

For best results, clean and dry skin before use. Test on a small area for allergies before use. Discontinue if irritation occurs. Apply a thick layer of the mask onto the face and neck avoiding the delicate eye area. Let the mask sit for 20~30 minutes depending on your skin type. Thoroughly rinse with warm water.